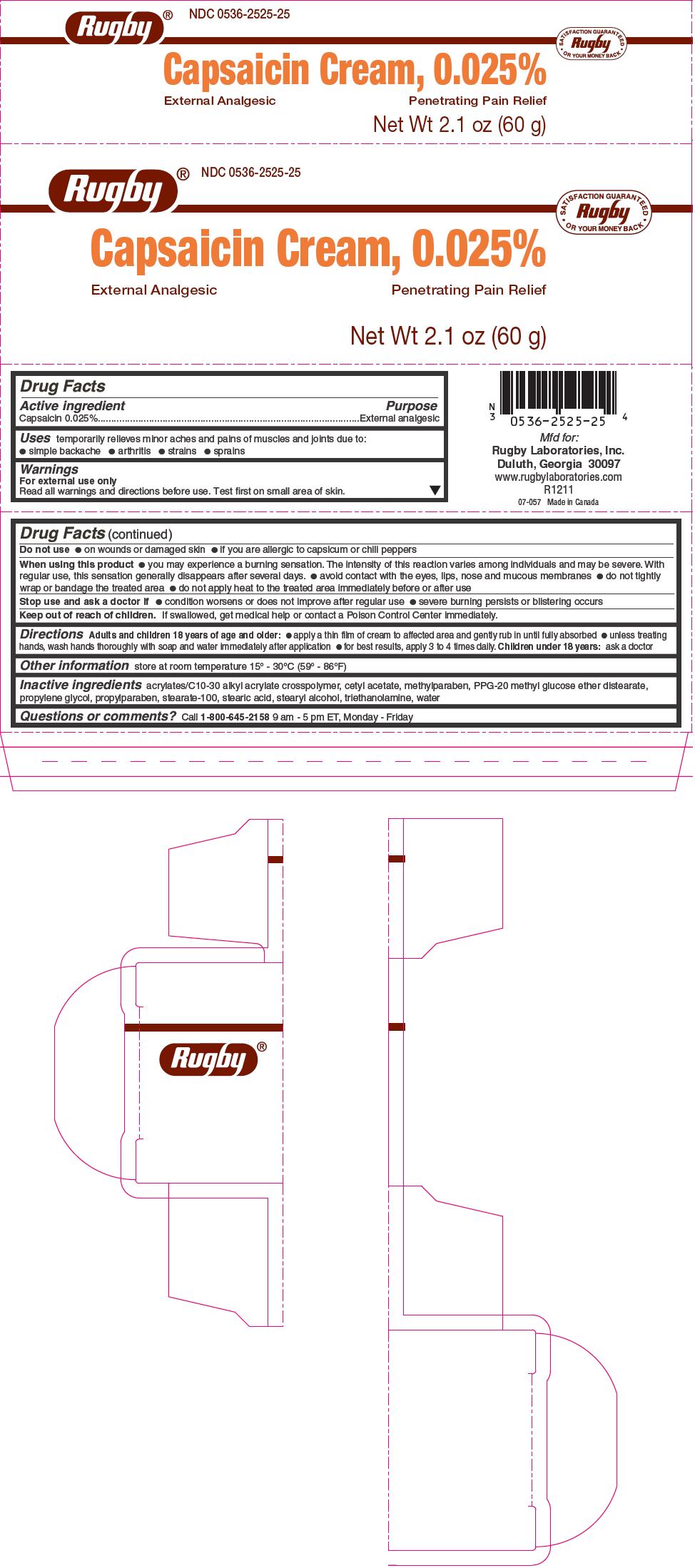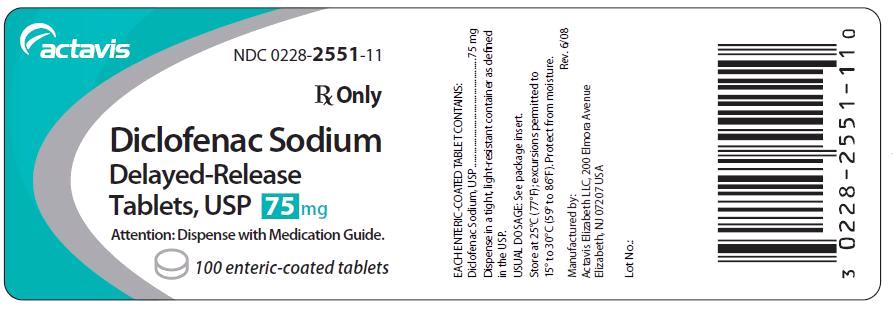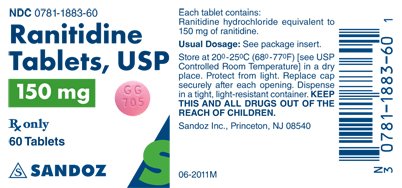 DRUG LABEL: Inflammation Reduction Pack
NDC: 69176-010 | Form: KIT | Route: TOPICAL
Manufacturer: TMIG, Inc.
Category: prescription | Type: HUMAN PRESCRIPTION DRUG LABEL
Date: 20150818

ACTIVE INGREDIENTS: CAPSAICIN 0.025 g/100 g; DICLOFENAC SODIUM 75 mg/1 1; RANITIDINE HYDROCHLORIDE 150 mg/1 1
INACTIVE INGREDIENTS: PPG-20 METHYL GLUCOSE ETHER DISTEARATE; CETYL ACETATE; PROPYLENE GLYCOL; STEARETH-100; STEARIC ACID; STEARYL ALCOHOL; TROLAMINE; WATER; CARBOMER COPOLYMER TYPE A (ALLYL PENTAERYTHRITOL CROSSLINKED); PROPYLPARABEN; METHYLPARABEN; POLYSORBATE 80; SODIUM ALGINATE; STEARIC ACID; FERROSOFERRIC OXIDE; TITANIUM DIOXIDE; HYPROMELLOSES; LACTOSE MONOHYDRATE; MAGNESIUM STEARATE; POLYETHYLENE GLYCOLS; PROPYLENE GLYCOL; SILICON DIOXIDE; TALC; SODIUM STARCH GLYCOLATE TYPE A POTATO; CELLULOSE, MICROCRYSTALLINE; PEPPERMINT; SODIUM STARCH GLYCOLATE TYPE A POTATO; TRIETHYL CITRATE; D&C RED NO. 30; HYDROXYPROPYL CELLULOSE (TYPE H); HYPROMELLOSE 2910 (3 MPA.S); MAGNESIUM STEARATE; CELLULOSE, MICROCRYSTALLINE; TITANIUM DIOXIDE

Inflamation Reduction Pack

Kit Description

Capsaicin Cream 0.025%

Ranitidine Tablet USP 150mg

Diclofenac Sodium Tablet 75mg

Ranitidine hydrochloride

Ranitidine hydrochloride (HCl), is a histamine H2-receptor antagonist. Chemically it is N-[2-[[[5-[(dimethylamino)methyl]-2-furanyl]methyl]thio]ethyl]-N’-methyl-2-nitro-1,1-ethenediamine, HCl.

It has the following structure:

ranitidine hydrochloride chemical structure
The empirical formula is C13H22N4O3S • HCl, representing a molecular weight of 350.87.

Ranitidine HCl is a white to pale yellow, granular substance that is soluble in water. It has a slightly bitter taste and sulfur like odor.

Each tablet, for oral administration contains 168 mg or 336 mg of ranitidine hydrochloride equivalent to 150 mg and 300 mg of ranitidine, respectively. Inactive ingredients: D & C Red #30 Aluminum Lake, hydroxypropyl cellulose, hydroxypropyl methylcellulose, magnesium stearate, microcrystalline cellulose, triethyl citrate, sodium starch glycolate, titanium dioxide and flavoring. The 300 mg also contains: D & C Yellow #10 Aluminum Lake.

Each capsule, for oral administration contains 168 mg or 336 mg of ranitidine hydrochloride equivalent to 150 mg and 300 mg of ranitidine, respectively. Inactive ingredients: Ammonium hydroxide, colloidal silicon dioxide, corn starch, FD & C Blue #1, FD & C Red #40, FD & C Yellow #6, gelatin, magnesium stearate, pharmaceutical glaze, propylene glycol, silicon dioxide, simethicone, sodium lauryl sulfate, sodium starch glycolate, and titanium dioxide.

Diclofenac sodium

Diclofenac sodium delayed-release tablets, USP are a benzeneacetic acid derivative. The chemical name is 2-[(2,6-dichlorophenyl)amino] benzeneacetic acid, monosodium salt. The molecular weight is 318.13. Its molecular formula is C14H10Cl2NNaO2, and it has the following structural formula

78e77986-figure-01
Each enteric-coated tablet for oral administration contains 50 mg or 75 mg of diclofenac sodium, USP. In addition, each tablet contains the following inactive ingredients: aluminum hydrate, colloidal silicon dioxide, hypromellose, lactose monohydrate, magnesium stearate, microcrystalline cellulose, polyethylene glycol, polysorbate 80, polyvinyl acetate phthalate, propylene glycol, silica, sodium alginate, sodium starch glycolate (Type A), stearic acid, synthetic black iron oxide, talc, and titanium dioxide.

Capsaisin 0.025%

For external use only
Read all warnings and directions before use. Test first on small area of skin.
Do not use
on wounds or damaged skin
if you are allergic to capsicum or chili peppers
When using this product
you may experience a burning sensation. The intensity of this reaction varies among individuals and may be severe. With regular use, this sensation generally disappears after several days.
avoid contact with the eyes, lips, nose and mucous membranes
do not tightly wrap or bandage the treated area
do not apply heat to the treated area immediately before or after use
Stop use and ask a doctor if
condition worsens or does not improve after regular use
severe burning persists or blistering occurs
Keep out of reach of children. If swallowed, get medical help or contact a Poison Control Center immediately.

Diclofenac Sodium

Cardiovascular Effects
Cardiovascular Thrombotic Events

Clinical trials of several COX-2 selective and nonselective NSAIDs of up to three years duration have shown an increased risk of serious cardiovascular (CV) thrombotic events, myocardial infarction, and stroke, which can be fatal. All NSAIDs, both COX-2 selective and nonselective, may have a similar risk. Patients with known CV disease or risk factors for CV disease may be at greater risk. To minimize the potential risk for an adverse CV event in patients treated with an NSAID, the lowest effective dose should be used for the shortest duration possible. Physicians and patients should remain alert for the development of such events, even in the absence of previous CV symptoms. Patients should be informed about the signs and/or symptoms of serious CV events and the steps to take if they occur.

There is no consistent evidence that concurrent use of aspirin mitigates the increased risk of serious CV thrombotic events associated with NSAID use. The concurrent use of aspirin and an NSAID does increase the risk of serious GI events (see WARNINGS, GI EFFECTS).

Two large, controlled, clinical trials of a COX-2 selective NSAID for the treatment of pain in the first 10-14 days following CABG surgery found an increased incidence of myocardial infarction and stroke (see CONTRAINDICATIONS).

Hypertension
NSAIDs can lead to onset of new hypertension or worsening of pre-existing hypertension, either of which may contribute to the increased incidence of CV events. Patients taking thiazides or loop diuretics may have impaired response to these therapies when taking NSAIDs. NSAIDs, including diclofenac sodium delayed-release tablets, USP should be used with caution in patients with hypertension. Blood pressure (BP) should be monitored closely during the initiation of NSAID treatment and throughout the course of therapy.

Congestive Heart Failure and Edema
Fluid retention and edema have been observed in some patients taking NSAIDs. Diclofenac sodium delayed-release should be used with caution in patients with fluid retention or heart failure.

Gastrointestinal (GI) Effects - Risk Of GI Ulceration, Bleeding, And Perforation
NSAIDs, including diclofenac sodium delayed-release, can cause serious gastrointestinal (GI) adverse events including inflammation, bleeding, ulceration, and perforation of the stomach, small intestine, or large intestine, which can be fatal. These serious adverse events can occur at any time, with or without warning symptoms, in patients treated with NSAIDs. Only one in five patients, who develop a serious upper GI adverse event on NSAID therapy, is symptomatic. Upper GI ulcers, gross bleeding, or perforation caused by NSAIDs occur in approximately 1% of patients treated for 3-6 months, and in about 2%-4% of patients treated for one year. These trends continue with longer duration of use, increasing the likelihood of developing a serious GI event at some time during the course of therapy. However, even short-term therapy is not without risk.

NSAIDs should be prescribed with extreme caution in those with a prior history of ulcer disease or gastrointestinal bleeding. Patients with a prior history of peptic ulcer disease and/or gastrointestinal bleeding who use NSAIDs have a greater than 10-fold increased risk for developing a GI bleed compared to patients with neither of these risk factors. Other factors that increase the risk for GI bleeding in patients treated with NSAIDs include concomitant use of oral corticosteroids or anticoagulants, longer duration of NSAID therapy, smoking, use of alcohol, older age, and poor general health status. Most spontaneous reports of fatal GI events are in elderly or debilitated patients and therefore, special care should be taken in treating this population.

To minimize the potential risk for an adverse GI event in patients treated with an NSAID, the lowest effective dose should be used for the shortest possible duration. Patients and physicians should remain alert for signs and symptoms of GI ulceration and bleeding during NSAID therapy and promptly initiate additional evaluation and treatment if a serious GI adverse event is suspected. This should include discontinuation of the NSAID until a serious GI adverse event is ruled out. For high risk patients, alternate therapies that do not involve NSAIDs should be considered.

Renal Effects
Caution should be used when initiating treatment with diclofenac sodium delayed-release in patients with considerable dehydration.

Long-term administration of NSAIDs has resulted in renal papillary necrosis and other renal injury. Renal toxicity has also been seen in patients in whom renal prostaglandins have a compensatory role in the maintenance of renal perfusion. In these patients, administration of a nonsteroidal anti-inflammatory drug may cause a dose-dependent reduction in prostaglandin formation and, secondarily, in renal blood flow, which may precipitate overt renal decompensation. Patients at greatest risk of this reaction are those with impaired renal function, heart failure, liver dysfunction, those taking diuretics and ACE inhibitors, and the elderly. Discontinuation of NSAID therapy is usually followed by recovery to the pretreatment state.

Advanced Renal Disease

No information is available from controlled clinical studies regarding the use of diclofenac sodium delayed-release in patients with advanced renal disease. Therefore, treatment with diclofenac sodium delayed-release is not recommended in these patients with advanced renal disease. If diclofenac sodium delayed-release therapy must be initiated, close monitoring of the patient's renal function is advisable.

Hepatic Effects
Elevations of one or more liver tests may occur during therapy with diclofenac sodium delayed-release. These laboratory abnormalities may progress, may remain unchanged, or may be transient with continued therapy. Borderline elevations (i.e., less than 3 times the ULN [ULN = the upper limit of the normal range]) or greater elevations of transaminases occurred in about 15% of diclofenac-treated patients. Of the markers of hepatic function, ALT (SGPT) is recommended for the monitoring of liver injury.

In clinical trials, meaningful elevations (i.e., more than 3 times the ULN) of AST (GOT) (ALT was not measured in all studies) occurred in about 2% of approximately 5,700 patients at some time during diclofenac treatment. In a large, open-label, controlled trial of 3,700 patients treated for 2-6 months, patients were monitored first at 8 weeks and 1,200 patients were monitored again at 24 weeks. Meaningful elevations of ALT and/or AST occurred in about 4% of patients and included marked elevations (i.e., more than 8 times the ULN) in about 1% of the 3,700 patients. In that open-label study, a higher incidence of borderline (less than 3 times the ULN), moderate (3-8 times the ULN), and marked (>8 times the ULN) elevations of ALT or AST was observed in patients receiving diclofenac when compared to other NSAIDs. Elevations in transaminases were seen more frequently in patients with osteoarthritis than in those with rheumatoid arthritis.

Almost all meaningful elevations in transaminases were detected before patients became symptomatic. Abnormal tests occurred during the first 2 months of therapy with diclofenac in 42 of the 51 patients in all trials who developed marked transaminase elevations.

In postmarketing reports, cases of drug-induced hepatotoxicity have been reported in the first month, and in some cases, the first 2 months of therapy, but can occur at any time during treatment with diclofenac. Postmarketing surveillance has reported cases of severe hepatic reactions, including liver necrosis, jaundice, fulminant hepatitis with and without jaundice, and liver failure. Some of these reported cases resulted in fatalities or liver transplantation.

Physicians should measure transaminases periodically in patients receiving long-term therapy with diclofenac, because severe hepatotoxicity may develop without a prodrome of distinguishing symptoms. The optimum times for making the first and subsequent transaminase measurements are not known. Based on clinical trial data and postmarketing experiences, transaminases should be monitored within 4 to 8 weeks after initiating treatment with diclofenac. However, severe hepatic reactions can occur at any time during treatment with diclofenac.

If abnormal liver tests persist or worsen, if clinical signs and/or symptoms consistent with liver disease develop, or if systemic manifestations occur (e.g., eosinophilia, rash, abdominal pain, diarrhea, dark urine, etc.), diclofenac sodium delayed-release should be discontinued immediately.

To minimize the possibility that hepatic injury will become severe between transaminase measurements, physicians should inform patients of the warning signs and symptoms of hepatotoxicity (e.g., nausea, fatigue, lethargy, diarrhea, pruritus, jaundice, right upper quadrant tenderness, and "flu-like" symptoms), and the appropriate action patients should take if these signs and symptoms appear.

To minimize the potential risk for an adverse liver related event in patients treated with diclofenac sodium delayed-release, the lowest effective dose should be used for the shortest duration possible. Caution should be exercised in prescribing diclofenac sodium delayed-release with concomitant drugs that are known to be potentially hepatotoxic (e.g., antibiotics, anti-epileptics).

Anaphylactic Reactions
As with other NSAIDs, anaphylactic reactions may occur both in patients with the aspirin triad and in patients without known sensitivity to NSAIDs or known prior exposure to diclofenac sodium delayed-release. Diclofenac sodium delayed-release should not be given to patients with the aspirin triad. This symptom complex typically occurs in asthmatic patients who experience rhinitis with or without nasal polyps, or who exhibit severe, potentially fatal bronchospasm after taking aspirin or other NSAIDs. (See CONTRAINDICATIONS and PRECAUTIONS, PREEXISTING ASTHMA.) Anaphylaxis-type reactions have been reported with NSAID products, including with diclofenac products, such as diclofenac sodium delayed-release. Emergency help should be sought in cases where an anaphylactic reaction occurs.

Skin Reactions
NSAIDs, including diclofenac sodium delayed-release, can cause serious skin adverse events such as exfoliative dermatitis, Stevens-Johnson Syndrome (SJS), and toxic epidermal necrolysis (TEN), which can be fatal. These serious events may occur without warning. Patients should be informed about the signs and symptoms of serious skin manifestations and use of the drug should be discontinued at the first appearance of skin rash or any other sign of hypersensitivity.

Pregnancy
In late pregnancy, as with other NSAIDs, diclofenac sodium delayed-release should be avoided because it may cause premature closure of the ductus arteriosus.

Ranitdine

Ranitidine is a competitive, reversible inhibitor of the action of histamine at the histamine H2-receptors, including receptors on the gastric cells. Ranitidine does not lower serum Ca++ in hypercalcemic states. Ranitidine is not a anticholinergic agent.

Pharmacokinetics
Absorption

Ranitidine tablets and ranitidine capsules are 50% absorbed after oral administration, compared to an intravenous (IV) injection with mean peak levels of 440 to 545 ng/mL occurring 2 to 3 hours after a 150 mg dose. Absorption is not significantly impaired by the administration of food or antacids. Propantheline slightly delays and increases peak blood levels of ranitidine, probably by delaying gastric emptying and transit time. In one study, simultaneous administration of high-potency antacid (150 mmol) in fasting subjects has been reported to decrease the absorption of ranitidine.

Distribution

The volume of distribution is about 1.4 L/kg. Serum protein binding averages 15%.

Metabolism

In humans, the N-oxide is the principal metabolite in the urine; however, this amounts to <4% of the dose. Other metabolites are the S-oxide (1%) and the desmethyl ranitidine (1%). The remainder of the administered dose is found in the stool. Studies in patients with hepatic dysfunction (compensated cirrhosis) indicate that there are minor, but clinically insignificant, alterations in ranitidine half-life, distribution, clearance, and bioavailability.

Excretion

The principal route of excretion is the urine, with approximately 30% of the orally administered dose collected in the urine as unchanged drug in 24 hours. Renal clearance is about 410 mL/min, indicating active tubular excretion. The elimination half-life is 2.5 to 3 hours. Four patients with clinically significant renal function impairment (creatinine clearance 25 to 35 mL/min) administered 50 mg of ranitidine intravenously had an average plasma half-life of 4.8 hours, a ranitidine clearance of 29 mL/min, and a volume of distribution of 1.76 L/kg. In general, these parameters appear to be altered in proportion to creatinine clearance (see DOSAGE AND ADMINISTRATION).

Geriatrics

The plasma half-life is prolonged and total clearance is reduced in the elderly population due to a decrease in renal function. The elimination half-life is 3 to 4 hours. Peak levels average 526 ng/mL following a 150 mg twice daily dose and occur in about 3 hours (see PRECAUTIONS: GERIATRIC USE and DOSAGE AND ADMINISTRATION: DOSAGE ADJUSTMENT FOR PATIENTS WITH IMPAIRED RENAL FUNCTION).

Pediatrics

There are no significant differences in the pharmacokinetic parameter values for ranitidine in pediatric patients (from 1 month up to 16 years of age) and healthy adults when correction is made for body weight. The average bioavailability of ranitidine given orally to pediatric patients is 48% which is comparable to the bioavailability of ranitidine in the adult population. All other pharmacokinetic parameter values (t1/2, Vd, and CL) are similar to those observed with intravenous ranitidine use in pediatric patients. Estimates of Cmax and Tmax are displayed in Table 1.

Ranitdine

Ranitidine is indicated in:

Short-term treatment of active duodenal ulcer. Most patients heal within 4 weeks. Studies available to date have not assessed the safety of ranitidine in uncomplicated duodenal ulcer for periods of more than 8 weeks.
Maintenance therapy for duodenal ulcer patients at reduced dosage after healing of acute ulcers. No placebo-controlled comparative studies have been carried out for periods of longer than 1 year.
The treatment of pathological hypersecretory conditions (e.g., Zollinger-Ellison syndrome and systemic mastocytosis).
Short-term treatment of active, benign gastric ulcer. Most patients heal within 6 weeks and the usefulness of further treatment has not been demonstrated. Studies available to date have not assessed the safety of ranitidine in uncomplicated, benign gastric ulcer for periods of more than 6 weeks.
Maintenance therapy for gastric ulcer patients at reduced dosage after healing of acute ulcers. Placebo-controlled studies have been carried out for 1 year.
Treatment of GERD. Symptomatic relief commonly occurs within 24 hours after starting therapy with ranitidine 150 mg two times a day.
Treatment of endoscopically diagnosed erosive esophagitis. Symptomatic relief of heartburn commonly occurs within 24 hours of therapy initiation with ranitidine 150 mg 4 times daily.
Maintenance of healing of erosive esophagitis. Placebo-controlled trials have been carried out for 48 weeks.
Concomitant antacids should be given as needed for pain relief to patients with active duodenal ulcer; active, benign gastric ulcer; hypersecretory states; GERD; and erosive esophagitis.

Ranitdine

Active Duodenal Ulcer
The current recommended adult oral dosage of ranitidine for duodenal ulcer is 150 mg twice daily. An alternative dosage of 300 mg once daily after the evening meal or at bedtime can be used for patients in whom dosing convenience is important. The advantages of one treatment regimen compared to the other in a particular patient population have yet to be demonstrated (see CLINICAL PHARMACOLOGY: CLINICAL TRIALS: ACTIVE DUODENAL ULCER). Smaller doses have been shown to be equally effective in inhibiting gastric acid secretion in US studies, and several foreign trials have shown that 100 mg twice daily is as effective as the 150 mg dose.

Antacid should be given as needed for relief of pain (see CLINICAL PHARMACOLOGY: PHARMACOKINETICS).